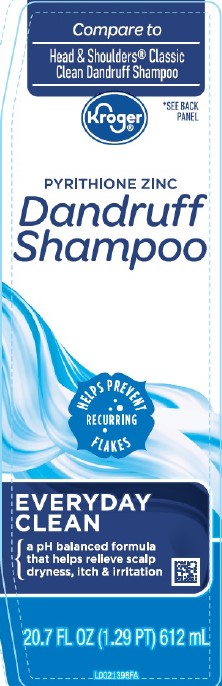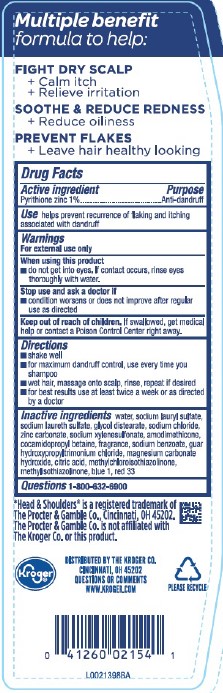 DRUG LABEL: Everyday Clean Dandruff
NDC: 30142-153 | Form: SHAMPOO
Manufacturer: The Kroger Co.
Category: otc | Type: HUMAN OTC DRUG LABEL
Date: 20260227

ACTIVE INGREDIENTS: PYRITHIONE ZINC 10 mg/1 mL
INACTIVE INGREDIENTS: WATER; SODIUM LAURYL SULFATE; SODIUM LAURETH SULFATE; GLYCOL DISTEARATE; SODIUM CHLORIDE; ZINC CARBONATE; SODIUM XYLENESULFONATE; AMODIMETHICONE (800 CST); COCAMIDOPROPYL BETAINE; SODIUM BENZOATE; GUAR HYDROXYPROPYLTRIMONIUM CHLORIDE (1.7 SUBSTITUENTS PER SACCHARIDE); MAGNESIUM CARBONATE HYDROXIDE; CITRIC ACID MONOHYDRATE; METHYLCHLOROISOTHIAZOLINONE; METHYLISOTHIAZOLINONE; FD&C BLUE NO. 1; D&C RED NO. 33

Kroger 153.008/153BD
Everyday Clean Dandruff Shampoo

Claims

Multiple benefitformula to help:

FIGHT DRY SCALP

+ Calm itch

+ Relieve irritation

SOOTHE & REDUCE REDNESS

+ Reduce oiliness

PREVENT FLAKES

+ Leaves hair healthy looking

Acitve ingredient

Pyrithione zinc 1%

Purpose

Anti-dandruff

Use

helps prevent recurrence of flaking and itching associated with dandruff

Warnings

For external use only

When using this product

- do not get into eyes. If contact occurs, rinse eyes thoroughly with water.

Stop use and ask a doctor if

- condition worsens or does not improve after regular use as directed

Keep out of reach of children.

If swallowed, get medical help or contact a Poison Control Center right away.

Directions

- shake well
- for maximum dandruff control, use every time you shampoo
- wet hair, massage onto scalp, rinse, repeat if desired
- for best results use at least twice a week or as directed by a doctor

Inactive ingredients

water, sodium lauryl sulfate, sodium laureth sulfate, glycol distearate, sodium chloride, zinc carbonate, sodium xylenesulfonate, amodimethicone, cocamidopropyl betaine, fragrance, sodium benzoate, guar hydroxypropyltrimonium chloride, magnesium carbonate hydroxide, citric acid, methylchloroisothiazolinone, methylisothiazolinone, blue 1, red 33

Questions

1-800-632-6900

Disclaimer

*Head & Shoulders®is a registered trademark of The Procter & Gamble Co., Cincinnati, OH 45202.

The Procter & Gamble Co. is not affiliated with The Kroger Co. or this product.

Adverse reaction

DISTRIBUTED BY THE KROGER CO.

CINCINNATI, OH 45202

QUESTIONS OR COMMENTS

WWW.KROGER.COM

KROGER®

PLEASE RECYCLE

PRINCIPAL DISPLAY PANEL

Compare to Head & Shoulders®Classic Clean Dandruff Shampoo

Kroger®

*SEE BACK PANEL

PYRITHIONE ZINC

Dandruff Shampoo

HELPS PREVENT RECURRING FLAKES

EVERYDAY CLEAN

a pH balanced formula that helps relieve scalp dryness, itch & irriataion

20.7 FL OZ (1.29 PT) 612 mL